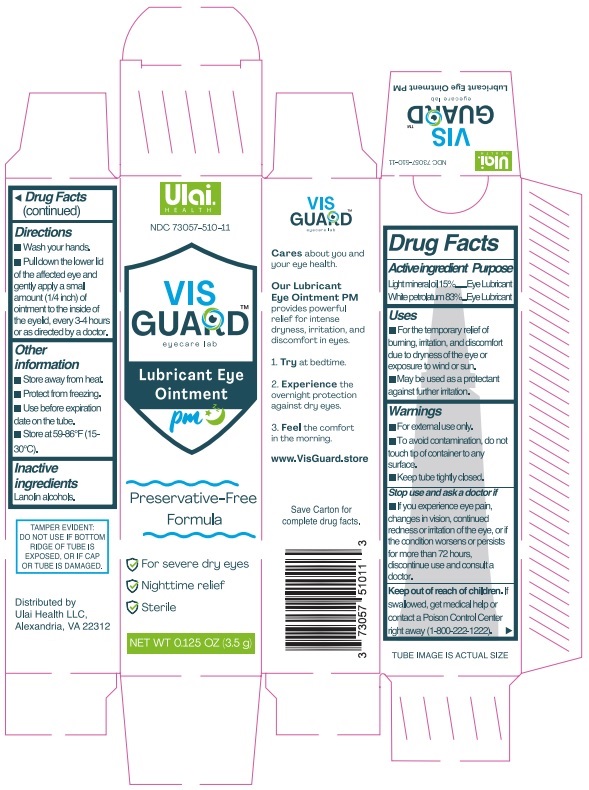 DRUG LABEL: Vis Guard Lubricant EyeOintment PM
NDC: 73057-510 | Form: OINTMENT
Manufacturer: Ulai Health LLC
Category: otc | Type: HUMAN OTC DRUG LABEL
Date: 20260113

ACTIVE INGREDIENTS: PETROLATUM 830 mg/1 g; LIGHT MINERAL OIL 150 mg/1 g
INACTIVE INGREDIENTS: LANOLIN ALCOHOLS 20 mg/1 g

Active Ingredients

Light Mineral oil 15%...........................................Lubricant

White petrolatum 83%.........................................Lubricant

Purposes

Lubricant

Uses

■ For the temporary relief of burning, irritation, and discomfort due to dryness of the eye or exposure to wind or sun.

■ May be used as a protectant against further irritation.

Warnings

■ For external use only.
■ To avoid contamination, do not touch tip of container to any surface.
■ Keep tube tightly closed.

Stop use and ask a doctor if

■ If you experience eye pain, changes in vision, continued redness or irritation of the eye, or if the condition worsens or persists
for more than 72 hours, discontinue use and consult a doctor.

Keep out of reach of Children

If swallowed, get medical help or contact a Poison Control Center right away (1-800-222-1222).

Direction

■ Wash your hands.

■Pull down the lower lid of the affected eye and gently apply a small amount (1/4 inch) of ointment to the inside of the eyelid, every 3-4 hours or as directed by a doctor.

Other Information

■ Store away from heat.
■ Protect from freezing.
■ Use before expiration date on the tube.
■ Store at 59-86°F (15-30°C).

Inactive Ingredients

Lanolin alcohols.